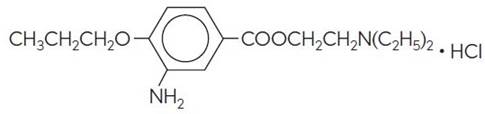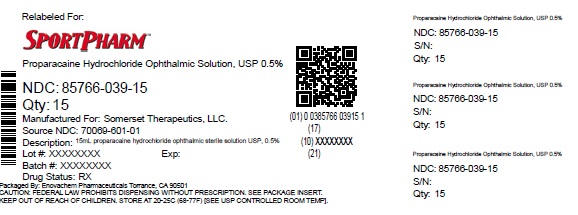 DRUG LABEL: Proparacaine Hydrochloride
NDC: 85766-039 | Form: SOLUTION/ DROPS
Manufacturer: Sportpharm LLC
Category: prescription | Type: HUMAN PRESCRIPTION DRUG LABEL
Date: 20260206

ACTIVE INGREDIENTS: PROPARACAINE HYDROCHLORIDE 5 mg/1 mL
INACTIVE INGREDIENTS: BENZALKONIUM CHLORIDE; GLYCERIN; HYDROCHLORIC ACID; SODIUM HYDROXIDE; WATER

Proparacaine Hydrochloride Ophthalmic Solution, USP 0.5%
(Sterile)
Rx only

DESCRIPTION

Proparacaine hydrochloride ophthalmic solution USP, 0.5% is a local anesthetic for ophthalmic instillation. Each mL of sterile, aqueous solution contains: Active:Proparacaine Hydrochloride 5 mg (0.5%). Preservative:Benzalkonium Chloride 0.1 mg (0.01%). Inactives:Glycerin as a stabilizer, Hydrochloric Acid and/or Sodium Hydroxide may be added to adjust pH, and Water for Injection USP.

Proparacaine hydrochloride is designated chemically as 2-(Diethylamino) ethyl 3-amino-4- propoxybenzoate monohydrochloride.

C16H26N2O3•HCl

MW 330.85

CAS-5875-06-9

CLINICAL PHARMACOLOGY

Proparacaine Hydrochloride Ophthalmic Solution is a rapid acting local anesthetic suitable for ophthalmic use. With a single drop, the onset of anesthesia occurs in approximately 13 seconds and persists for 15 minutes or longer.

The main site of anesthetic action is the nerve cell membrane where proparacaine interferes with the large transient increase in the membrane permeability to sodium ions that is normally produced by a slight depolarization of the membrane. As the anesthetic action progressively develops in a nerve, the threshold for electrical stimulation gradually increases and the safety factor for conduction decreases; when this action is sufficiently well developed, block of conduction is produced.

The exact mechanism whereby proparacaine and other local anesthetics influence the permeability of the cell membrane is unknown; however, several studies indicate that local anesthetics may limit sodium ion permeability by closing the pores through which the ions migrate in the lipid layer of the nerve cell membrane. This limitation prevents the fundamental change necessary for the generation of the action potential.

INDICATIONS AND USAGE

Proparacaine Hydrochloride Ophthalmic Solution is indicated for topical anesthesia in ophthalmic practice. Representative ophthalmic procedures in which the preparation provides good local anesthesia include measurement of intraocular pressure (tonometry), removal of foreign bodies and sutures from the cornea, conjunctival scraping in diagnosis and gonioscopic examination; it is also indicated for use as a topical anesthetic prior to surgical operations such as cataract extraction.

CONTRAINDICATIONS

This preparation is contraindicated in patients with known hypersensitivity to any component of the solution.

WARNINGS

NOT FOR INJECTION INTO THE EYE - For topical ophthalmic use only.

Prolonged use of a topical ocular anesthetic may produce permanent corneal opacification with accompanying loss of vision.

Proparacaine ophthalmic solution is indicated for administration under the direct supervision of a healthcare provider. Proparacaine ophthalmic solution is not intended for patient self-administration.

PRECAUTIONS

General

Proparacaine should be used cautiously and sparingly in patients with known allergies, cardiac disease, or hyperthyroidism. The long-term toxicity of proparacaine is unknown; prolonged use may possibly delay wound healing. Although exceedingly rare with ophthalmic application of local anesthetics, it should be borne in mind that systemic toxicity (manifested by central nervous system stimulation followed by depression) may occur.

Protection of the eye from irritating chemicals, foreign bodies and rubbing during the period of anesthesia is very important. Tonometers soaked in sterilizing or detergent solutions should be thoroughly rinsed with sterile distilled water prior to use. Patients should be advised to avoid touching the eye until the anesthesia has worn off.

Carcinogenesis, Mutagenesis, Impairment of Fertility

Long-term studies in animals have not been performed to evaluate carcinogenic potential, mutagenicity or possible impairment of fertility in males or females.

Pregnancy

Animal reproduction studies have not been conducted with proparacaine hydrochloride ophthalmic solution 0.5%. It is also not known whether proparacaine hydrochloride can cause fetal harm when administered to a pregnant woman or can affect reproduction capacity. Proparacaine hydrochloride should be administered to a pregnant woman only if clearly needed.

Nursing Mothers

It is not known whether this drug is excreted in human milk. Because many drugs are excreted in human milk, caution should be exercised when proparacaine hydrochloride is administered to a nursing woman.

Pediatric Use

Safety and effectiveness of proparacaine hydrochloride ophthalmic solution in pediatric patients have been established. Use of proparacaine hydrochloride is supported by evidence from adequate and well-controlled studies in adults and children over the age of twelve, and safety information in neonates and other pediatric patients.

Geriatric Use

No overall clinical differences in safety of effectiveness have been observed between the elderly and other adult patients.

ADVERSE REACTIONS

Pupillary dilation or cycloplegic effects have rarely been observed with proparacaine hydrochloride. The drug appears to be safe for use in patients sensitive to other local anesthetics, but local or systemic sensitivity occasionally occurs.

Instillation of proparacaine in the eye at recommended concentration and dosage usually produces little or no initial irritation, stinging, burning, conjunctival redness, lacrimation or increased winking. However, some local irritation and stinging may occur several hours after the instillation. Rarely, a severe, immediate-type, apparently hyperallergic corneal reaction may occur which includes acute, intense and diffuse epithelial keratitis; a gray, ground glass appearance; sloughing of large areas of necrotic epithelium; corneal filaments and, sometimes, iritis with descemetitis. Allergic contact dermatitis with drying and fissuring of the fingertips has been reported.

Softening and erosion of the corneal epithelium and conjunctival congestion and hemorrhage have been reported.

To report SUSPECTED ADVERSE REACTIONS, contact Somerset Therapeutics, LLC at 1- 800-417-9175 or FDA at 1-800 -FDA-1088 orwww.fda.gov/medwatch

DOSAGE AND ADMINISTRATION

Deep anesthesia as in cataract extraction:

Instill 1 drop every 5 to 10 minutes for 5 to 7 doses.

Removal of sutures:

Instill 1 or 2 drops 2 or 3 minutes before removal of stitches.

Removal of foreign bodies:

Instill 1 or 2 drops prior to operating.

Tonometry:

Instill 1 or 2 drops immediately before measurement.

FOR TOPICAL OPHTHALMIC USE ONLY

HOW SUPPLIED

Proparacaine Hydrochloride Ophthalmic Solution USP, 0.5% is supplied as a sterile solution in a 15 mL white LDPE bottle with natural LDPE nozzle and white HDPE cap as follows:

NDC 85766-039-15, 15 mL fill in a 15 mL capacity bottle (relabeled from NDC 70069-601-01)

Storage:

Refrigerate at 2° to 8° C (36°F to 46°F). Keep bottle tightly closed. Store bottles in carton until empty to protect from light. If solution shows more than a faint yellow color, it should not be used.

Keep out of reach of children.

SPL UNCLASSIFIED

Distributed by:

Sportpharm LLC
379 Van Ness Ave 1401,
Torrance, CA 90501

Relabeled by:

Enovachem PHARMACEUTICALS

Torrance, CA 90501